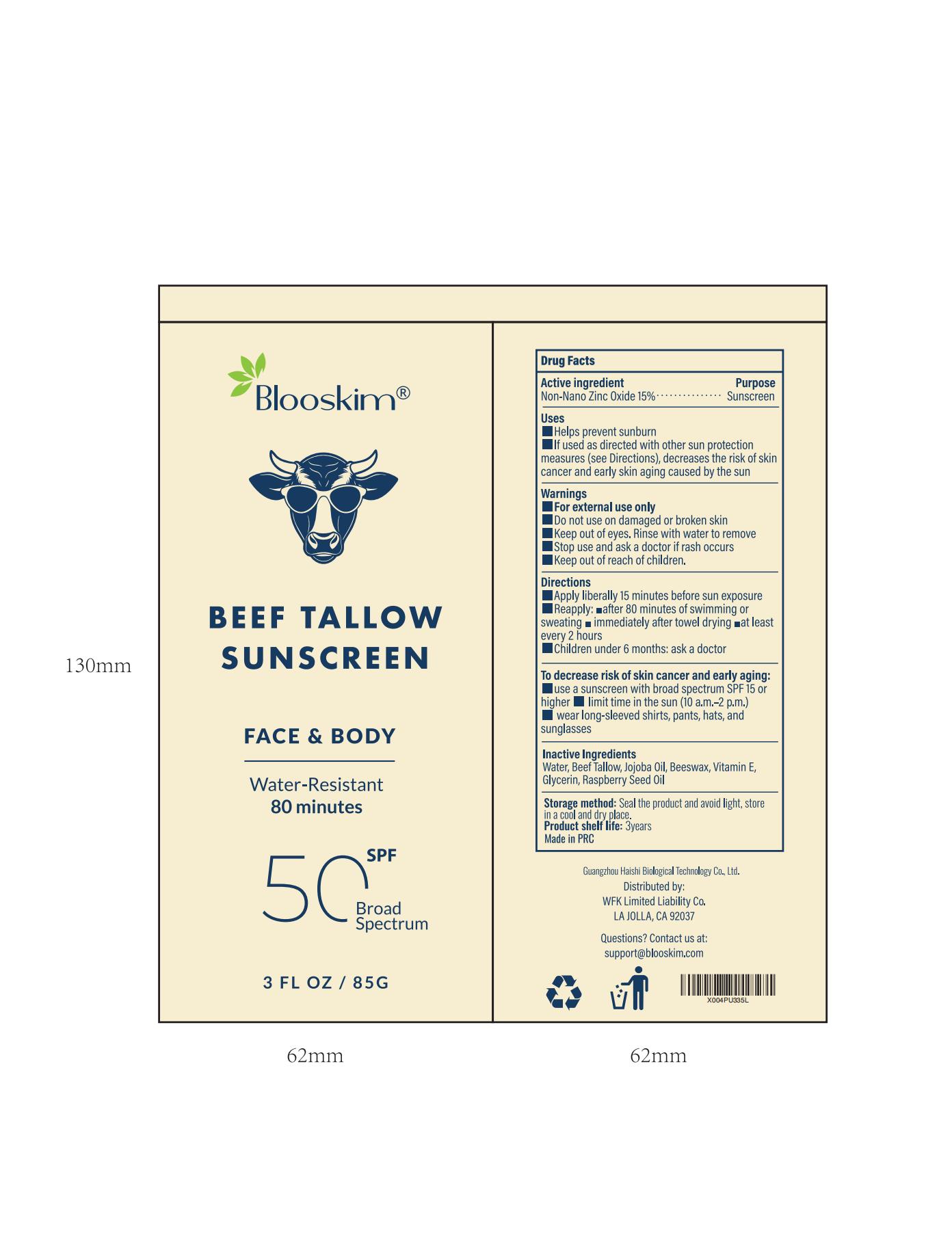 DRUG LABEL: Blooskim BEEF TALLOW SUNSCREEN
NDC: 60771-0022 | Form: CREAM
Manufacturer: Guangzhou Haishi Biological Technology Co., Ltd.
Category: otc | Type: HUMAN OTC DRUG LABEL
Date: 20250624

ACTIVE INGREDIENTS: ZINC OXIDE 15 g/100 mL
INACTIVE INGREDIENTS: JOJOBA OIL; BEEF TALLOW; BEESWAX; GLYCERIN

Blooskim@ BEEF TALLOW SUNSCREEN

Active ingredient

Non-Nano Zinc Oxide 15%

Purpose

sunscreen

Uses

Apply liberally 15 minutes before sun exposure

Warnings

For external use only.

Stop use and ask a doctor if

rash occurs.

Do not use

on damaged or broken skin.

When using this product

keep out of eyes. Rinse with water to remove.

Keep out of reach of children.

If swallowed, get medical help or contact a Poison Control Center right away.

Dosage

Squeeze out an appropriate amount of product and spread evenly on skin.

Inactive ingredients

Water 33%
Beef Tallow 30%
Jojoba Oil 8%
Beeswax 5%
Vitamin E 2%
Glycerin 5%
Raspberry Seed 0il 2%